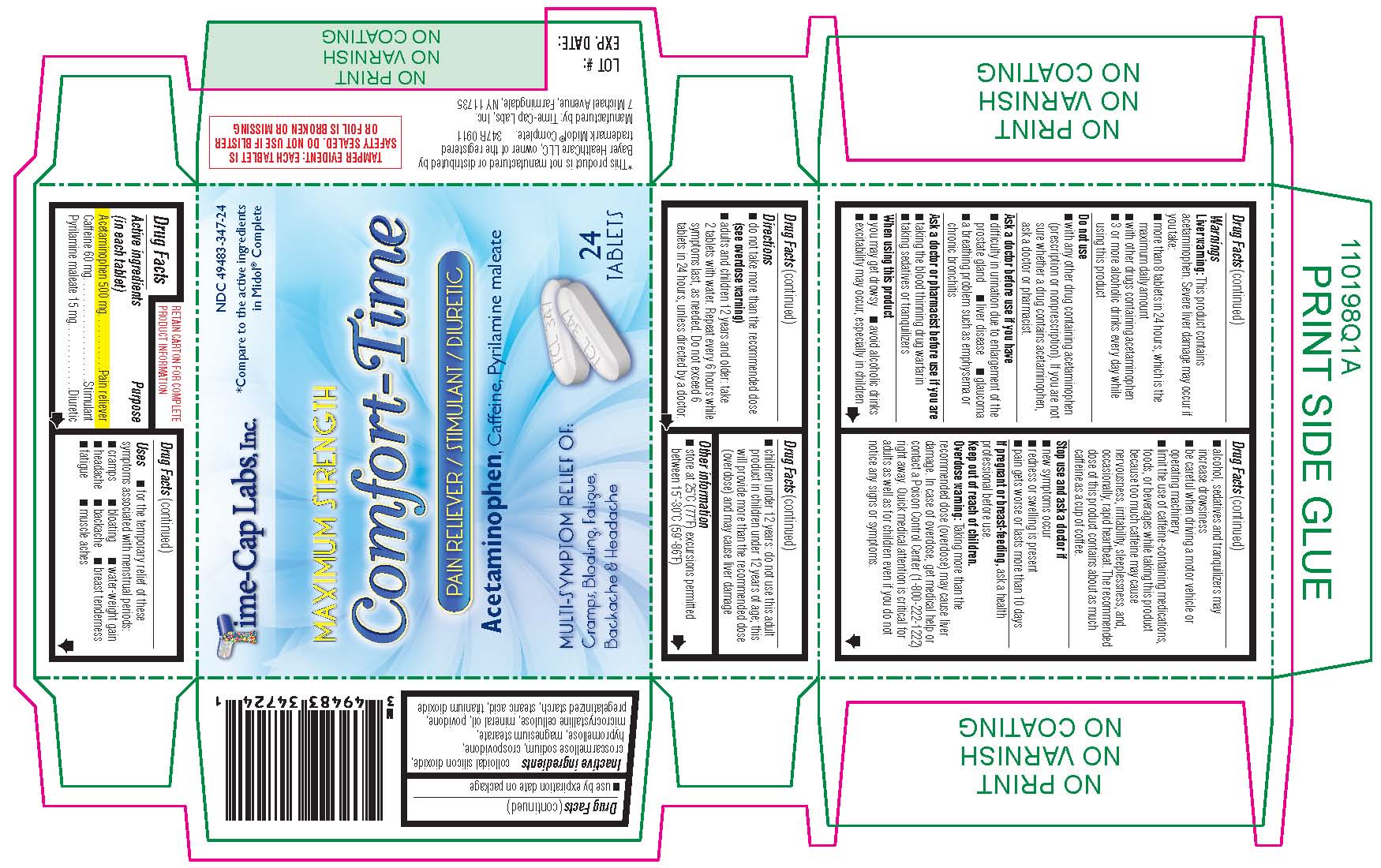 DRUG LABEL: Comfort-Time
NDC: 49483-347 | Form: TABLET, FILM COATED
Manufacturer: Time Cap Labs, Inc
Category: otc | Type: HUMAN OTC DRUG LABEL
Date: 20181214

ACTIVE INGREDIENTS: ACETAMINOPHEN 500 mg/1 1; CAFFEINE 60 mg/1 1; PYRILAMINE MALEATE 15 mg/1 1
INACTIVE INGREDIENTS: SILICON DIOXIDE; CROSCARMELLOSE SODIUM; CROSPOVIDONE; HYPROMELLOSE 2910 (6 MPA.S); HYPROMELLOSE 2910 (15 MPA.S); MAGNESIUM STEARATE; CELLULOSE, MICROCRYSTALLINE; MINERAL OIL; POVIDONE; STARCH, CORN; STEARIC ACID; TITANIUM DIOXIDE

TCL COMFORT TIME 347R

active ingredients (in each tablet)

Acetaminophen 500 mg
Caffeine 60 mg
Pyrilamine maleate 15 mg

PURPOSE

active ingredients (in each tablet)

Acetaminophen 500 mg
Caffeine 60 mg
Pyrilamine maleate 15 mg

Uses

for the temporary relief of these symptoms associated with menstrual periods:

cramps
bloating
water-weight gain
headache
backache
breast tenderness
fatigue
muscle aches

WARNINGS

-
  Warnings
  Liver warning:
  This product contains acetaminophen. Severe liver damage may occur if you take:
  more than 8 tablets in 24 hours, which is the maximum daily amount
  with other drugs containing acetaminophen
  3 or more alcoholic drinks every day while using this product

Do not use

with any other drug containing acetaminophen (prescription or nonprescription). If you are not sure whether a drug contains acetaminophen, ask a doctor or pharmacist.

Ask a doctor before use if you have

difficulty in urination due to enlargement of the prostate gland
liver disease
glaucoma
a breathing problem such as emphysema or chronic bronchitis

Ask a doctor or pharmacist before use if you are

taking the blood thinning drug warfarin
taking sedatives or tranquilizers

When using this product

you may get drowsy
avoid alcoholic drinks
excitability may occur, especially in children
alcohol, sedatives, and tranquilizers may increase drowsiness
be careful when driving a motor vehicle or operating machinery
limit the use of caffeine-containing medications, foods, or beverages while taking this product because too much caffeine may cause nervousness, irritability, sleeplessness, and, occasionally, rapid heartbeat. The recommended dose of this product contains about as much caffeine as a cup of coffee.

Stop use and ask a doctor if

new symptoms occur
redness or swelling is present
pain gets worse or lasts more than 10 days

If pregnant or breast-feeding,

ask a health professional before use.

Keep out of reach of children.

WARNINGS
Liver warning:

This product contains acetaminophen. Severe liver damage may occur if you take:

more than 8 tablets in 24 hours, which is the maximum daily amount
with other drugs containing acetaminophen
3 or more alcoholic drinks every day while using this product

Uses

for the temporary relief of these symptoms associated with menstrual periods:

cramps
bloating
water-weight gain
headache
backache
breast tenderness
fatigue
muscle aches

Other information

store at 25°C (77°F) excursions permitted between 15°-30°C (59°-86°F)
use by expiration date on package

Inactive ingredients

colloidal silicon dioxide, croscarmellose sodium, crospovidone, hypromellose, magnesium stearate, microcrystalline cellulose, mineral oil, povidone, pregelatinized starch, stearic acid, titanium dioxide